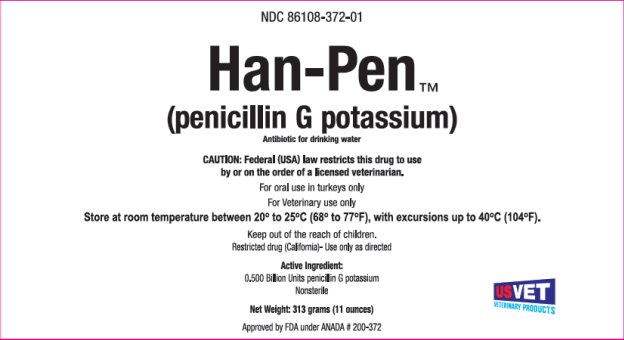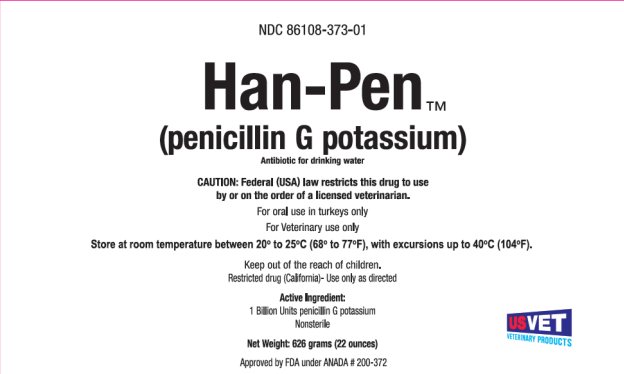 DRUG LABEL: Han-Pen
NDC: 86108-372 | Form: POWDER, FOR SOLUTION
Manufacturer: US Vet Inc
Category: animal | Type: PRESCRIPTION ANIMAL DRUG LABEL
Date: 20250314

ACTIVE INGREDIENTS: Penicillin G Potassium 500000000 [iU]/313 g

Han-Pen (penicillin G potassium)

DESCRIPTION

0.5 BU Front Panel

Penicillin G Potassium
Antibiotic for drinking water

CAUTION: Federal (USA) law restricts this drug to use by or on the order of a licensed veterinarian.

For oral use in turkeys only
For Veterinary use only
Store at room temperature between 20o to 25oC (68o to 77oF), with excursions up to 40oC (104oF).
Keep out of the reach of children.
Restricted drug (California) -Use only as directed
Active Ingredient:
0.500 Billion Units of penicillin G potassium
Nonsterile
Net Weight: 313 grams (11 ounces)
Approved by FDA under ANADA #200-372

INDICATIONS AND USAGE

For the treatment of erysipelas in turkeys (caused by Erysipelothrix rhusiopathiae).

DOSAGE AND ADMINISTRATION

Administer orally at a dosage of 1,500,000 units of penicillin per gallon (3.8 liters) of drinking water for 5 consecutive days.

Directions

Combine contents and approximately 1-1/2 pints (710 mL) of water in a glass or plastic container. Stir to dissolve. Allow concentrated solution to stand until the foam disappears. The concentrated solution should be used up or discarded within one hour after preparation.

Automatic Watering Systems - Pour the concentrated solution into a glass or plastic container then add enough water to make 2.6 gallons (9.9 liters) of stock solution. [This amount of solution will medicate 333 gallons (1260 liters) of drinking water]. The automatic waterer should be adjusted to deliver 1 ounce (30 mL) of stock solution per gallon (3.8 liters) of drinking water. In automatic watering systems, prepare fresh solutions daily.

Gravity Flow Watering Systems - Pour the concentrated solution into enough water to make 333 gallons (1260 liters) of drinking water. In gravity flow watering systems, prepare fresh solutions every 12 hours.

Drinking water prepared as directed above will contain 1,500,000 units of penicillin G per gallon (3.8 liters).

WARNINGS

Treated turkeys must not be slaughtered for food during treatment and for one day after last treatment. Do not use in turkeys producing eggs for human consumption.

PRECAUTIONS

For best results, the treatment should be started at the first sign of infection. If improvement is not noted after 3 to 4 days of treatment, consult a poultry pathologist or veterinarian.

DESCRIPTION

1 BU Front Panel

Penicillin G Potassium
Antibiotic for drinking water

CAUTION: Federal (USA) law restricts this drug to use by or on the order of a licensed veterinarian.

For oral use in turkeys only
For Veterinary use only
Store at room temperature between 20o to 25oC (68o to 77oF), with excursions up to 40oC (104oF).
Keep out of the reach of children.
Restricted drug (California) -Use only as directed
Active Ingredient:
1 Billion Units of penicillin G potassium
Nonsterile
Net Weight: 626 grams (22 ounces)
Approved by FDA under ANADA #200-372

INDICATIONS AND USAGE

For the treatment of erysipelas in turkeys (caused by Erysipelothrix rhusiopathiae).

DOSAGE AND ADMINISTRATION

Administer orally at a dosage of 1,500,000 units of penicillin per gallon (3.8 liters) of drinking water for 5 consecutive days.

Directions

Combine contents and approximately 3 pints (1420 mL) of water in a glass or plastic container. Stir to dissolve. Allow concentrated solution to stand until the foam disappears. The concentrated solution should be used up or discarded within one hour after preparation.

Automatic Watering Systems - Pour the concentrated solution into a glass or plastic container then add enough water to make 5.2 gallons (19.7 liters) of stock solution. [This amount of solution will medicate 666 gallons (2521 liters) of drinking water]. The automatic waterer should be adjusted to deliver 1 ounce (30 mL) of stock solution per gallon (3.8 liters) of drinking water. In automatic watering systems, prepare fresh solutions daily.

Gravity Flow Watering Systems - Pour the concentrated solution into enough water to make 666 gallons (2521 liters) of drinking water. In gravity flow watering systems, prepare fresh solutions every 12 hours.

Drinking water prepared as directed above will contain 1,500,000 units of penicillin G per gallon (3.8 liters).

WARNINGS

Treated turkeys must not be slaughtered for food during treatment and for one day after last treatment. Do not use in turkeys producing eggs for human consumption.

PRECAUTIONS

For best results, the treatment should be started at the first sign of infection. If improvement is not noted after 3 to 4 days of treatment, consult a poultry pathologist or veterinarian.

Manufactured for:
US VET Inc.
Liverpool, NY 13088

Rev. 08/2024

PACKAGE/LABEL PRINCIPAL DISPLAY PANEL

NDC 86108-372-01
Han-Pen ™
(penicillin G potassium)
Antibiotic for drinking water

PACKAGE/LABEL PRINCIPAL DISPLAY PANEL

NDC 86108-373-01
Han-Pen ™
(penicillin G potassium)
Antibiotic for drinking water